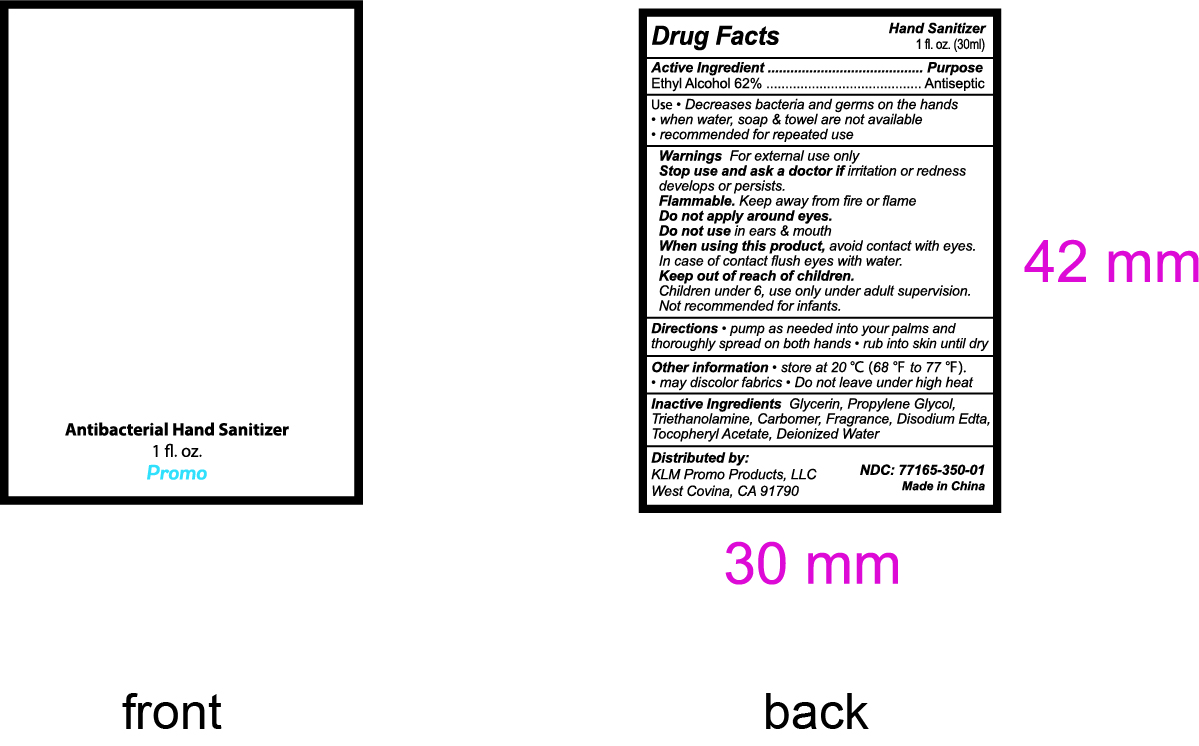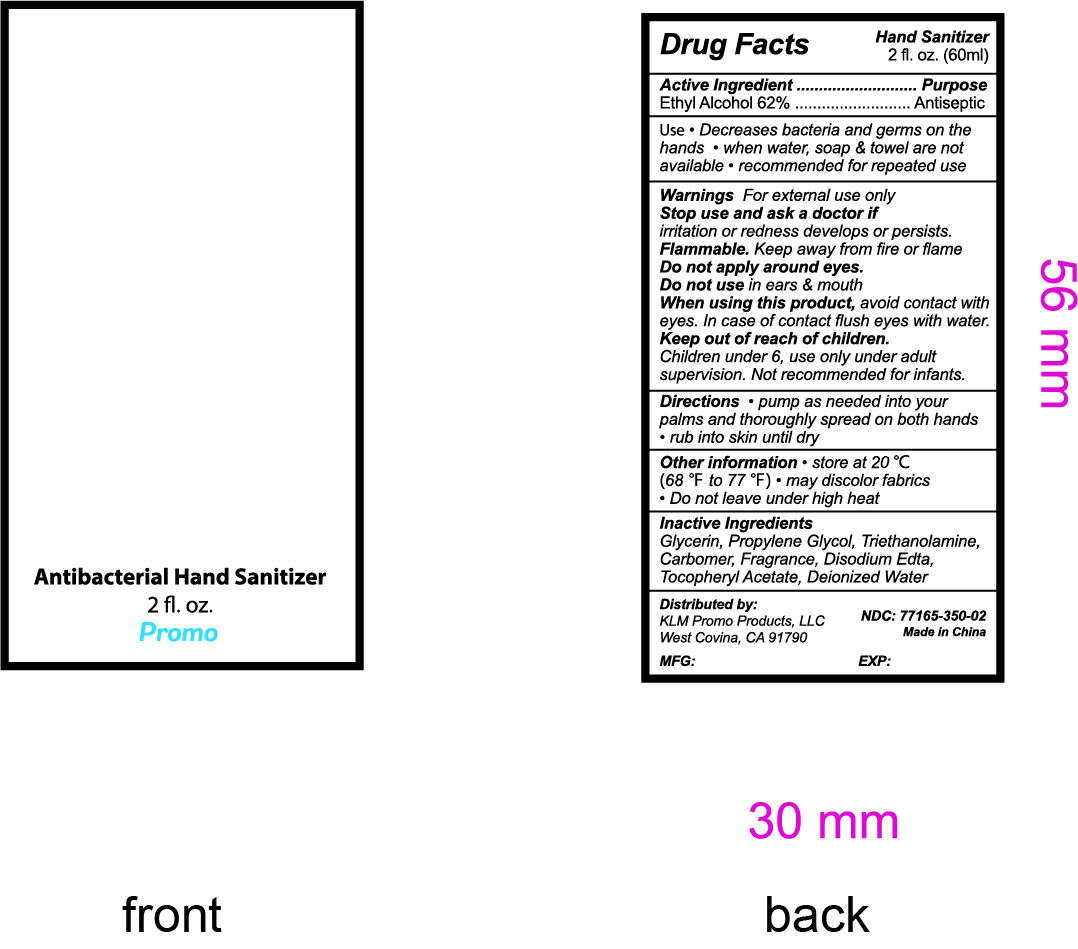 DRUG LABEL: Antibacterial Hand Sanitizer
NDC: 77165-350 | Form: LIQUID
Manufacturer: KLM Promo Products, LLC
Category: otc | Type: HUMAN OTC DRUG LABEL
Date: 20210109

ACTIVE INGREDIENTS: ALCOHOL 62 mL/100 mL
INACTIVE INGREDIENTS: .ALPHA.-TOCOPHEROL ACETATE, D-; CARBOMER HOMOPOLYMER, UNSPECIFIED TYPE; GLYCERIN; WATER; PROPYLENE GLYCOL; EDETATE DISODIUM; TROLAMINE

klm hand sanitizer

Active Ingredient(s)

Ethyl Alcohol 62%. Purpose: Antiseptic

Purpose

Antiseptic, Hand Sanitizer

Use

Decrease bacteria and germs on the hands
when water, soap, and towel are not available
recommended for repeated use

Warnings

For external use only.

Do not use in ears and mouth

When using this product avoid contact with eyes. In case of contact flush eyes with water.

Stop use and ask a doctor if irritation or redness develops or persists.

KEEP OUT OF REACH OF CHILDREN

Children under 6, use only under adult supervision. Not recommended for infants.

Directions

- pump as needed on to your palms and thoroughly spread on both hands
- rub into skin until dry

Other information

- store at 20℃(68℉-77℉)
- may discolor fabrics
- do not leave under high heat

Inactive ingredients

Glycerin, Propylene Glycol, Triethanolamine, Carbomer, Fragrance, Disodium EDTA , Tocopheryl Acetate, Deionized Water

Package Label - Principal Display Panel

30 mL NDC: 77165-350-01

antibacterial hand sanitizer

1 fl.oz. (30ml)